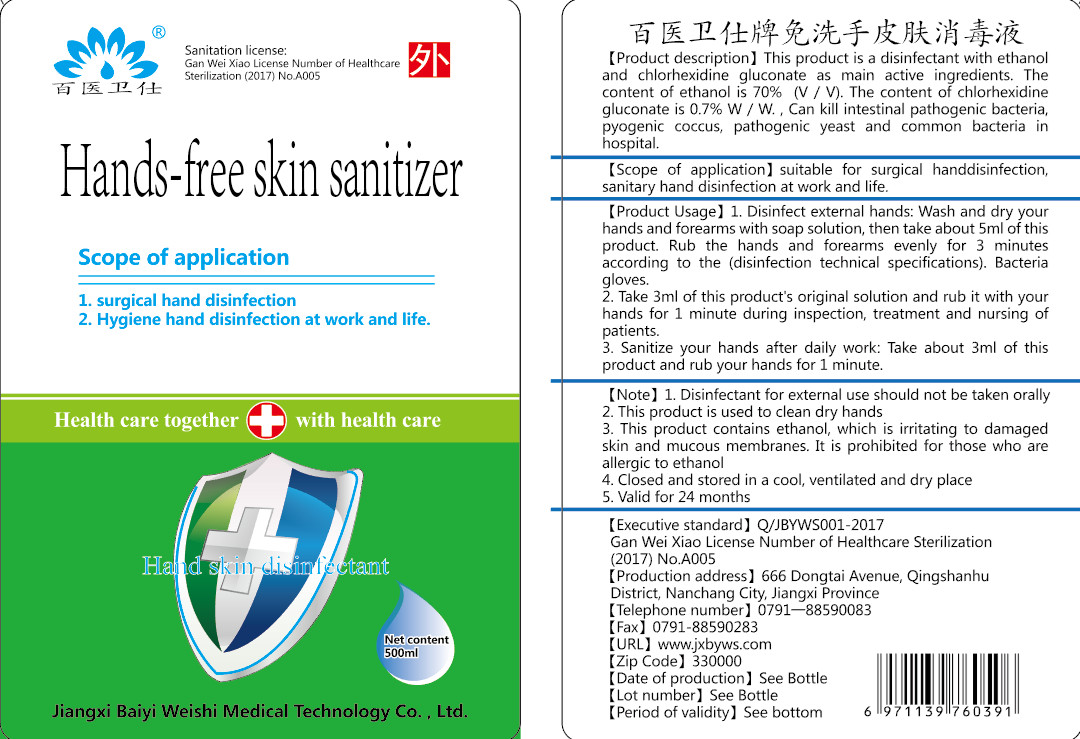 DRUG LABEL: Hands-free skin sanitizer
NDC: 40796-002 | Form: LIQUID
Manufacturer: Jiangxi Baiyi Weishi Medical Technology Co., Ltd.
Category: otc | Type: HUMAN OTC DRUG LABEL
Date: 20200513

ACTIVE INGREDIENTS: CHLORHEXIDINE GLUCONATE 3.5 g/500 mL; ALCOHOL 350 mL/500 mL
INACTIVE INGREDIENTS: WATER

DOSAGE AND ADMINISTRATION

Closed and stored in a cool, ventilated and dry place

INACTIVE INGREDIENT

Purified water

INDICATIONS AND USAGE

1. Disinfect external hands: Wash and dry your hands and forearms with soap solution, then take about 5ml of this product. Rub the hands and forearms evenly for 3 minutes according to the (disinfection technical specifications). Bacteria gloves.
2. Take 3ml of this product's original solution and rub it with your hands for 1 minute during inspection, treatment and nursing of patients.
3. Sanitize your hands after daily work: Take about 3ml of this product and rub your hands for 1 minute.

ACTIVE INGREDIENT

Ethanol

dextrose chlorhexidine

keep out of reach of children

PURPOSE

Disinfection
Sterilization
No Rinseing

WARNINGS

1. Disinfectant for external use should not be taken orally
2. This product is used to clean dry hands
3. This product contains ethanol, which is irritating to damaged skin and mucous membranes. It is prohibited for those who are allergic to ethanol
4. Closed and stored in a cool, ventilated and dry place
5. Valid for 24 months